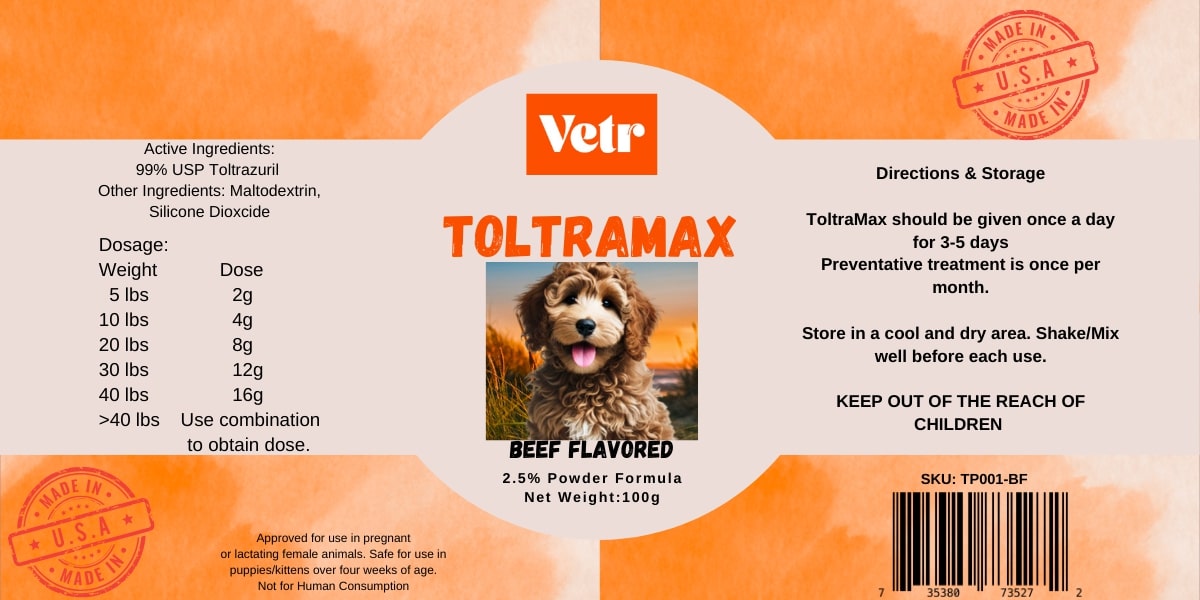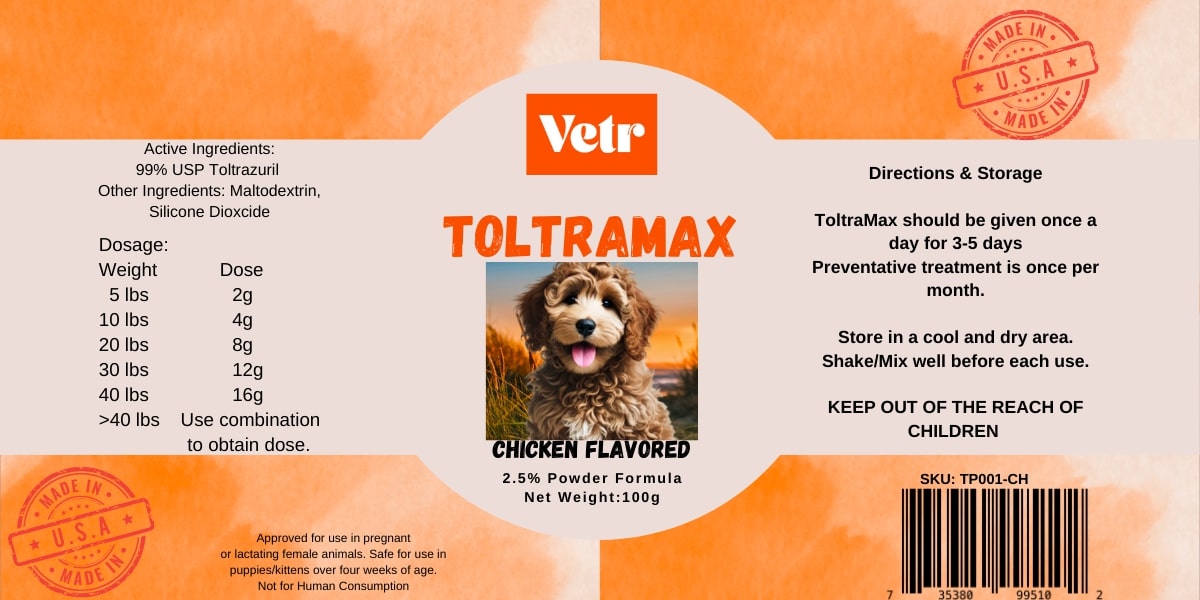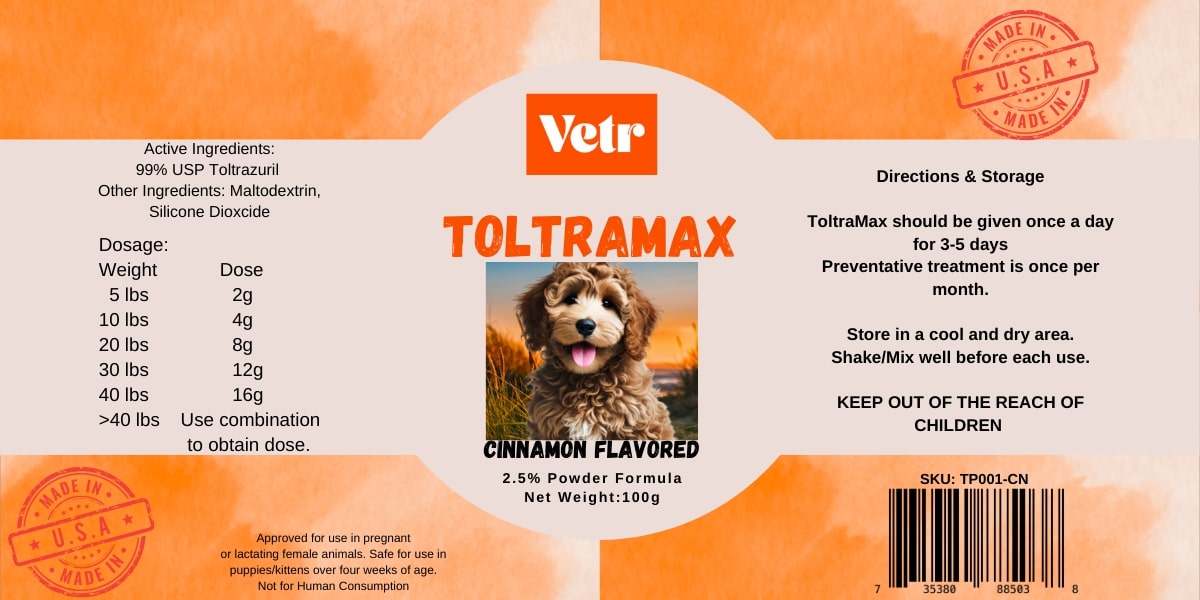 DRUG LABEL: Toltramax Powder 2.5%
NDC: 86213-131 | Form: POWDER
Manufacturer: Vetr, LLC
Category: animal | Type: OTC ANIMAL DRUG LABEL
Date: 20251214

ACTIVE INGREDIENTS: TOLTRAZURIL 25 mg/1 g
INACTIVE INGREDIENTS: MALTODEXTRIN; SILICON DIOXIDE

Toltramax 2.5% (2.5% toltrazuril, 25 mg/g)

Keep out of reach of children. Recognized as safe for use in pregnant and lactating females and puppies & kittens over four weeks of age.

DOSAGE AND ADMINISTRATION

Shake/mix well before use. Dose at 1 g of powder (25 mg toltrazuril) per 10 pounds of body weight, for 3-5 consecutive days. Toltramax should be administered orally and retreatment may be necessary after 4-6 weeks.

STORAGE AND HANDLING

Store at room temperature (at or below 77F).

ACTIVE INGREDIENT

Toltrazuril USP, 2.5% w/w (25 mg/g)

INACTIVE INGREDIENT

Maltodextrin, silicon dioxide, natural and artificial flavor